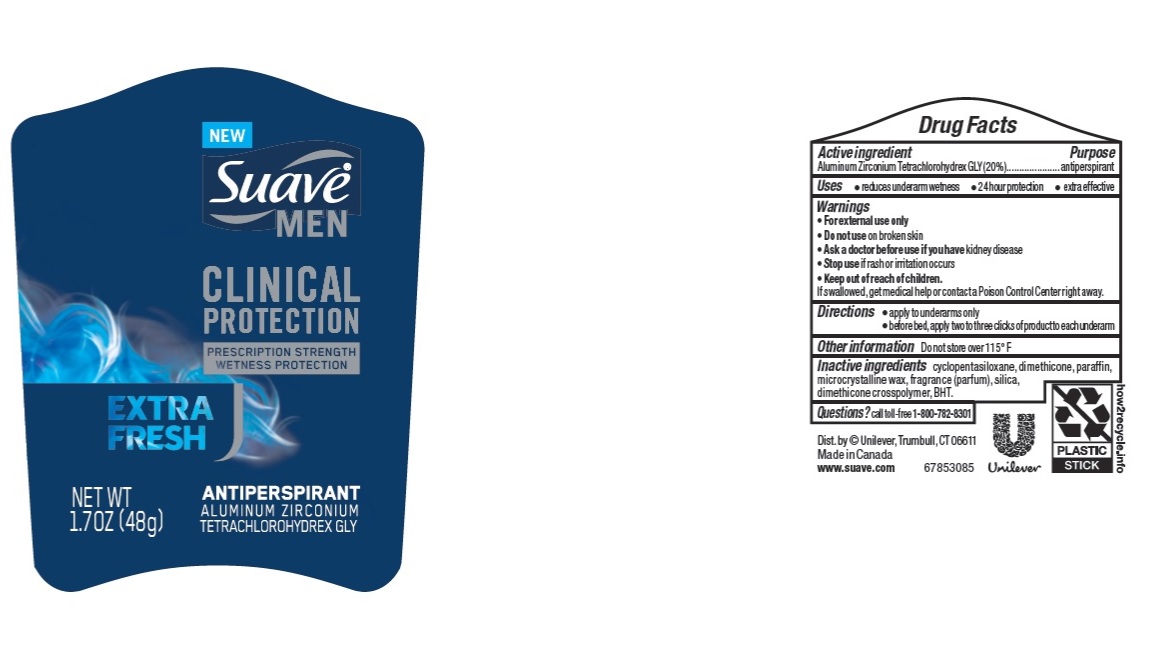 DRUG LABEL: Suave
NDC: 64942-1655 | Form: STICK
Manufacturer: Conopco Inc. d/b/a/ Unilever
Category: otc | Type: HUMAN OTC DRUG LABEL
Date: 20221207

ACTIVE INGREDIENTS: ALUMINUM ZIRCONIUM TETRACHLOROHYDREX GLY 20 g/100 g
INACTIVE INGREDIENTS: DIMETHICONE; MICROCRYSTALLINE WAX; PARAFFIN; CYCLOMETHICONE 5; BUTYLATED HYDROXYTOLUENE; SILICON DIOXIDE

Suave Men Clinical Protection Active Sport Antiperspirant

SUAVE MEN CLINICAL PROTECTION ACTIVE SPORT ANTIPERSPIRANT- aluminum zirconium tetrachlorohydrex gly stick

Suave Men Clinical Protection Ative Sport Antiperspirant

Drug Facts

Active ingredient

Aluminum Zirconium Tetrachlorohydrex GLY (20%)

Purpose

antiperspirant

Uses

• reduces underarm wetness
• 24 hour protection
• extra effective

Warnings

• For external use only.
• Do not use on broken skin .
• Ask a doctor before use if you have kidney disease.
• Stop use if rash or irritation occurs.

• Keep out of reach of children.

If swallowed, get medical help or contact a Poison Control Center right away.

Directions

• apply to underarms only
• before bed, apply two to three clicks of product to each underarm

Other information

Do not store over 115 °F

Inactive ingredients

Cyclopentasiloxane, Dimethicone, Paraffin, Microcrystalline Wax, Silica, Fragrance (Parfum), Dimethicone Crosspolymer, BHT.

Questions?

Call toll-free 1-800-782-8301